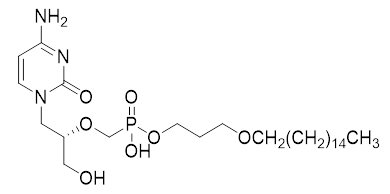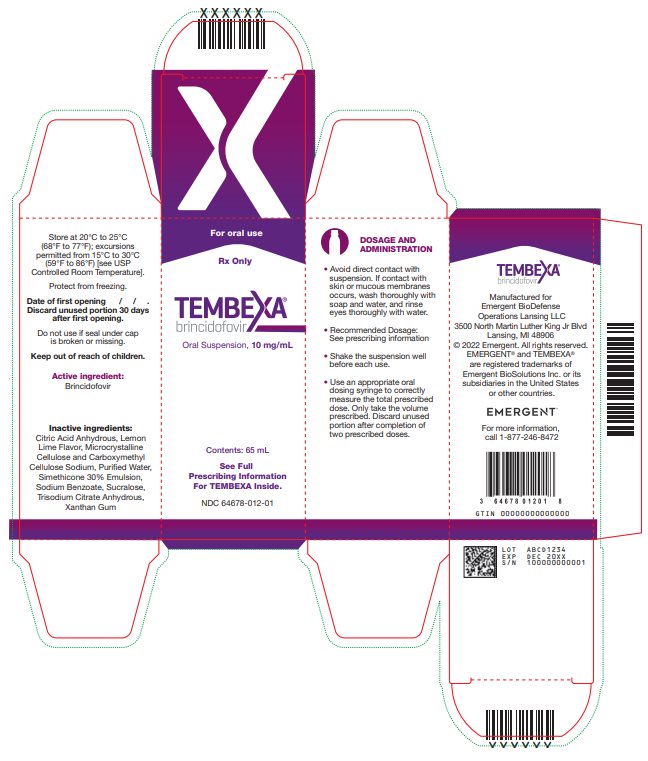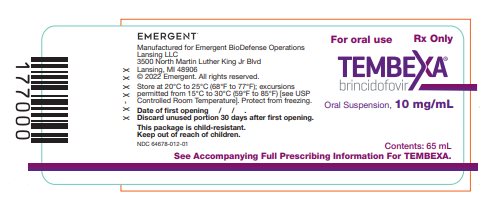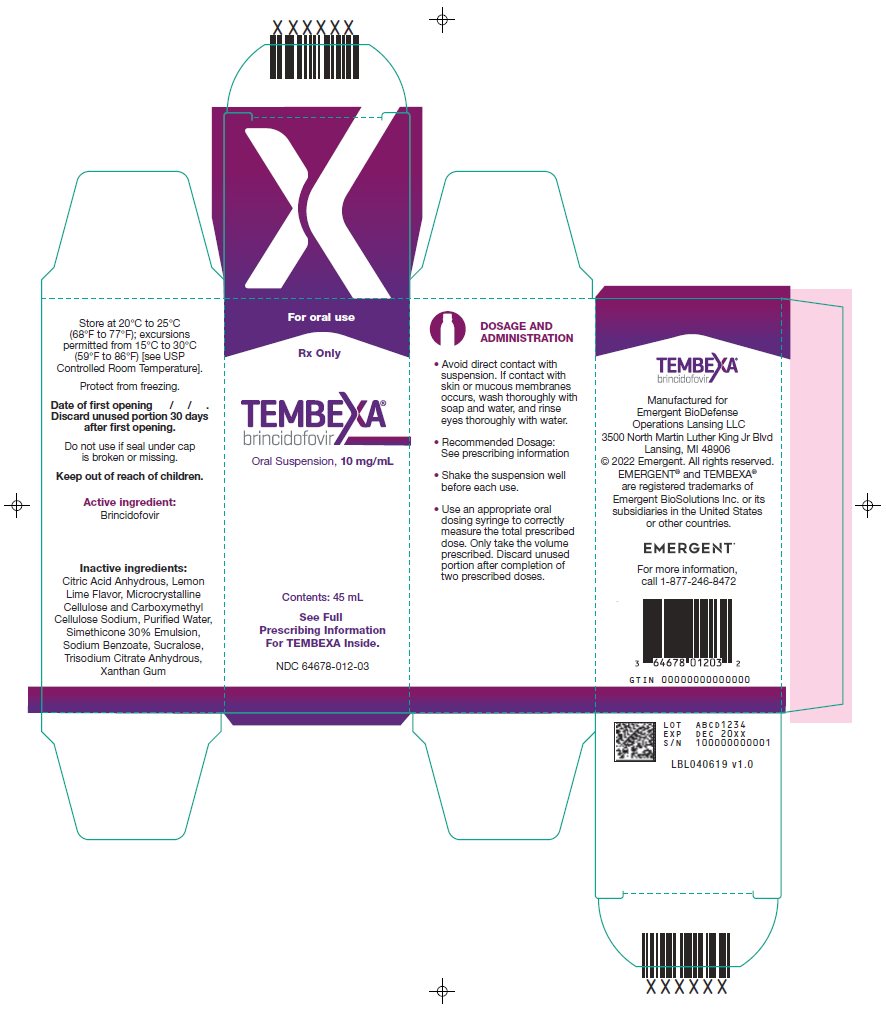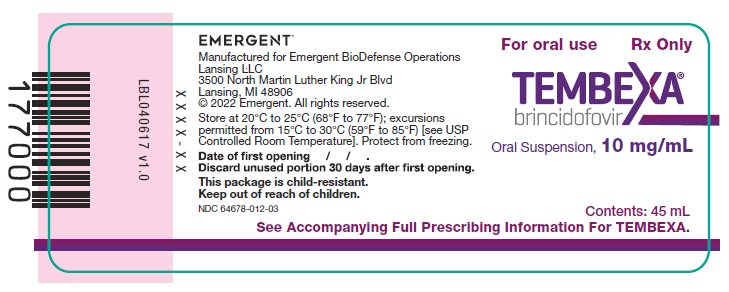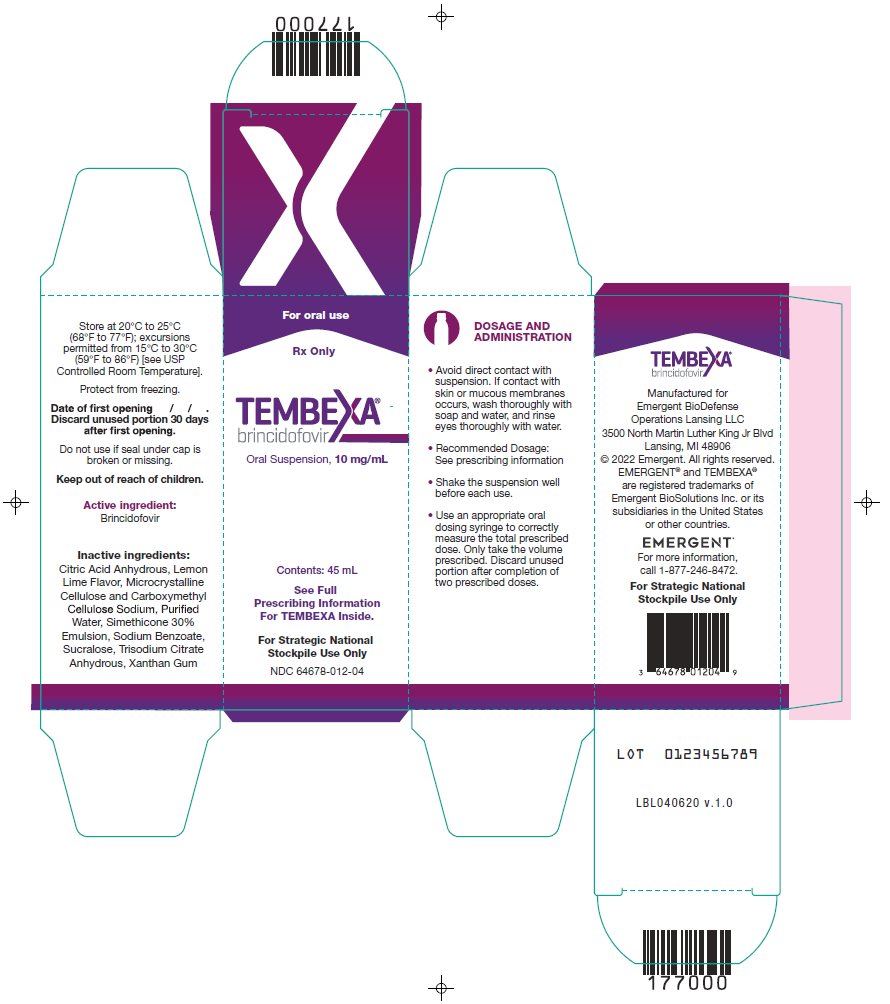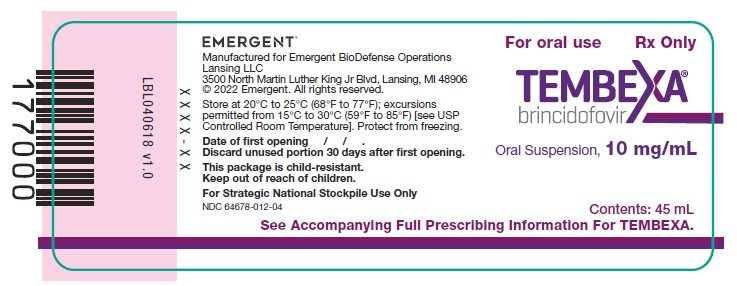 DRUG LABEL: Tembexa
NDC: 64678-012 | Form: SUSPENSION
Manufacturer: Emergent BioDefense Operations Lansing LLC
Category: prescription | Type: HUMAN PRESCRIPTION DRUG LABEL
Date: 20250723

ACTIVE INGREDIENTS: BRINCIDOFOVIR 10 mg/1 mL
INACTIVE INGREDIENTS: MICROCRYSTALLINE CELLULOSE; CARBOXYMETHYLCELLULOSE SODIUM, UNSPECIFIED; XANTHAN GUM; ANHYDROUS CITRIC ACID; ANHYDROUS TRISODIUM CITRATE; SODIUM BENZOATE; SUCRALOSE; WATER; SILICON DIOXIDE

HIGHLIGHTS OF PRESCRIBING INFORMATION

These highlights do not include all the information needed to use TEMBEXA® safely and effectively. See full prescribing information for TEMBEXA.
TEMBEXA (brincidofovir) tablets, for oral use
TEMBEXA (brincidofovir) oral suspension
Initial U.S. Approval: 1996

WARNING: INCREASED RISK FOR MORTALITY WHEN USED FOR LONGER DURATION

See full prescribing information for complete boxed warning.

An increased incidence of mortality was seen in TEMBEXA-treated subjects compared to placebo-treated subjects in a 24-week clinical trial when TEMBEXA was evaluated in another disease [see Warnings and Precautions (5.1)].

1 INDICATIONS AND USAGE

TEMBEXA is an orthopoxvirus nucleotide analog DNA polymerase inhibitor and is indicated for the treatment of human smallpox disease in adult and pediatric patients, including neonates. (1.1)

Limitations of Use:

- TEMBEXA is not indicated for the treatment of diseases other than human smallpox disease. (1.2)
- The effectiveness of TEMBEXA for treatment of smallpox disease has not been determined in humans because adequate and well-controlled field trials have not been feasible, and inducing smallpox disease in humans to study the drug’s efficacy is not ethical. (1.2)
- TEMBEXA efficacy may be reduced in immunocompromised patients based on studies in immune deficient animals. (1.2)

2 DOSAGE AND ADMINISTRATION

- Testing: Before initiation and during treatment with TEMBEXA perform hepatic laboratory testing and pregnancy testing. (2.1)
- See full prescribing information for details on important administration instructions. (2.2)
- Adult and pediatric patients weighing 48 kg or above: 200 mg (two 100 mg tablets or 20 mL oral suspension for patients who cannot swallow tablets) once weekly for 2 doses. (2.3)
- Adult and pediatric patients weighing 10 kg to less than 48 kg: 4 mg/kg oral suspension once weekly for 2 doses. (2.3)
- Pediatric patients weighing less than 10 kg: 6 mg/kg oral suspension once weekly for 2 doses. (2.3)

3 DOSAGE FORMS AND STRENGTHS

- Tablets: 100 mg (3)
- Oral Suspension: 10 mg/mL (3)

4 CONTRAINDICATIONS

None. (4)

5 WARNINGS AND PRECAUTIONS

- Elevations in Hepatic Transaminases and Bilirubin: May cause increases in serum transaminases (ALT or AST) and serum bilirubin. Monitor liver laboratory parameters before and during treatment. (5.2)
- Diarrhea and Other Gastrointestinal Adverse Events: Diarrhea and additional gastrointestinal adverse events including nausea, vomiting, and abdominal pain may occur. Monitor patients, provide supportive care, and if necessary, do not give the second and final dose of TEMBEXA. (5.3)
- Coadministration with Related Products: TEMBEXA should not be coadministered with intravenous cidofovir. (5.4)
- Embryo-fetal Toxicity: May cause fetal harm. Advise individuals of childbearing potential of the potential risk to the fetus and to use effective contraception. (5.5, 8.1, 8.3)
- Carcinogenicity: TEMBEXA should be considered a potential human carcinogen. Do not crush or divide TEMBEXA tablets. (5.6, 13.1)
- Male Infertility: Based on testicular toxicity in animal studies, TEMBEXA may irreversibly impair fertility in individuals of reproductive potential. (5.7, 8.3)

6 ADVERSE REACTIONS

Common adverse reactions (occurring in at least 2% of TEMBEXA-treated subjects) were diarrhea, nausea, vomiting, and abdominal pain. (6.1)

To report SUSPECTED ADVERSE REACTIONS, contact Emergent BioDefense Operations Lansing LLC at 1-877-246-8472 or FDA at 1-800-FDA-1088 or www.fda.gov/medwatch.

7 DRUG INTERACTIONS

Concomitant use with OATP1B1 and 1B3 inhibitors increase TEMBEXA exposure which may increase TEMBEXA-associated adverse reactions. Consider alternative medication that are not OATP1B1 or 1B3 inhibitors. If concomitant use is necessary, increase monitoring for adverse reactions associated with TEMBEXA and postpone the dosing of OATP1B1 or 1B3 inhibitors at least 3 hours after TEMBEXA administration. (7.1)

8 USE IN SPECIFIC POPULATIONS

- Lactation: Breastfeeding not recommended. (8.2)

FULL PRESCRIBING INFORMATION

WARNING: INCREASED RISK FOR MORTALITY WHEN USED FOR LONGER DURATION

An increased incidence of mortality was seen in TEMBEXA-treated subjects compared to placebo-treated subjects in a 24-week clinical trial when TEMBEXA was evaluated in another disease [see Warnings and Precautions (5.1)].

1 INDICATIONS AND USAGE

1.1 Treatment of Human Smallpox Disease

TEMBEXA® is indicated for the treatment of human smallpox disease caused by variola virus in adult and pediatric patients, including neonates.

1.2 Limitations of Use

TEMBEXA is not indicated for the treatment of diseases other than human smallpox disease [see Warnings and Precautions (5.1, 5.2)].

The effectiveness of TEMBEXA for the treatment of smallpox disease has not been determined in humans because adequate and well-controlled field trials have not been feasible, and inducing smallpox disease in humans to study the drug’s efficacy is not ethical [see Clinical Studies (14)].

TEMBEXA efficacy may be reduced in immunocompromised patients based on studies in immune deficient animals.

2 DOSAGE AND ADMINISTRATION

2.1 Testing Before Initiating and During Treatment with TEMBEXA

Perform hepatic laboratory testing in all patients before starting TEMBEXA and while receiving TEMBEXA, as clinically appropriate [see Warnings and Precautions (5.2) and Use in Specific Populations (8.7)].

Perform pregnancy testing before initiation of TEMBEXA in individuals of childbearing potential to inform risk [see Warnings and Precautions (5.5) and Use in Specific Populations (8.3)].

2.2 Important Administration Instructions

Avoid direct contact with broken or crushed tablets or oral suspension. If contact with skin or mucous membranes occurs, wash thoroughly with soap and water, and rinse eyes thoroughly with water [see Warnings and Precautions (5.6)].

TEMBEXA Tablets

TEMBEXA tablets can be taken on an empty stomach or with a low-fat meal (approximately 400 calories, with approximately 25% of calories from fat) [see Clinical Pharmacology (12.3)]. Swallow TEMBEXA tablets whole. Do not crush or divide TEMBEXA tablets.

TEMBEXA Oral Suspension

Take TEMBEXA oral suspension on an empty stomach [see Clinical Pharmacology (12.3)]. Shake oral suspension before use. Use an appropriate oral dosing syringe to correctly measure the total prescribed dose [see Patient Counseling Information (17)]. Discard unused portion after completion of 2 prescribed doses.

For patients who cannot swallow, TEMBEXA oral suspension can be administered by enteral tube (naso-gastric or gastrostomy tubes) as follows:

- Draw up prescribed dose with a calibrated catheter-tip syringe, and utilize this syringe to administer the dose via the enteral tube.
- Refill the catheter-tip syringe with 3 mL of water, shake, and administer the contents via the enteral tube.
- Flush with water before and after enteral administration.

2.3 Recommended Dosage

The recommended dosage of TEMBEXA in pediatric and adult patients is displayed in Table 1 [see Drug Interactions (7.1), Clinical Pharmacology (12.3) and Clinical Studies (14)].

Table 1: Recommended Dosage in Pediatric and Adult Patients
Patient’s Weight (kg) | TEMBEXA Oral Suspension; (10 mg/mL) | TEMBEXA Tablet; (100 mg)
Less than 10 kg | 6 mg/kg once weekly for 2 doses (on Days 1 and 8) | N/A
10 kg to less than 48 kg | 4 mg/kg once weekly for 2 doses (on Days 1 and 8) | N/A
48 kg and above | 200 mg (20 mL) once weekly for 2 doses (on Days 1 and 8) | 200 mg (two 100 mg tablets) once weekly for 2 doses (on Days 1 and 8)

3 DOSAGE FORMS AND STRENGTHS

Tablets

TEMBEXA tablets are blue, modified-oval shape, film-coated tablets debossed with BCV on one side and 100 on the other side. Each tablet contains 100 mg of brincidofovir.

Oral Suspension

TEMBEXA oral suspension is an aqueous based, preserved white to off-white opaque, lemon lime flavored suspension containing 10 mg/mL of brincidofovir.

4 CONTRAINDICATIONS

None.

5 WARNINGS AND PRECAUTIONS

5.1 Increased Risk for Mortality When Used for Longer Duration

TEMBEXA is not indicated for use in diseases other than human smallpox. An increase in mortality was observed in a randomized, placebo-controlled Phase 3 trial when TEMBEXA was evaluated in another disease. An increased risk in mortality is possible if TEMBEXA is used for a duration longer than at the recommended dosage on Days 1 and 8 [see Indications and Usage (1.2) and Dosage and Administration (2.3)].

Study 301 (CMX001-301) evaluated TEMBEXA versus placebo for the prevention of cytomegalovirus infection. A total of 303 subjects received TEMBEXA (100 mg twice weekly) and 149 subjects received matching placebo for up to 14 weeks. The primary endpoint was evaluated at Week 24. All-cause mortality at Week 24 was 16% in the TEMBEXA group compared to 10% in the placebo group. Safety and effectiveness of TEMBEXA have not been established for diseases other than human smallpox disease.

5.2 Elevations in Hepatic Transaminases and Bilirubin

Elevations in alanine aminotransferase (ALT), aspartate aminotransferase (AST), and total bilirubin have been observed, including cases of concurrent increases in ALT and bilirubin. During the first 2 weeks of TEMBEXA therapy in 392 subjects, ALT elevations >3x the upper limit of normal were reported in 7% of subjects and bilirubin elevations >2x the upper limit of normal were reported in 2% of subjects; these elevations in hepatic laboratory tests were generally reversible and did not require discontinuation of TEMBEXA [see Adverse Reactions (6.1) and Nonclinical Toxicology (13.2)]. Severe hepatobiliary adverse events including hyperbilirubinemia, acute hepatitis, hepatic steatosis, and venoocclusive liver disease have been reported in less than 1% of subjects.

Perform hepatic laboratory testing in all patients before starting TEMBEXA and while receiving TEMBEXA, as clinically appropriate. Monitor patients who develop abnormal hepatic laboratory tests during TEMBEXA therapy for the development of more severe hepatic injury. Consider discontinuing TEMBEXA if ALT levels remain persistently >10x the upper limit of normal. Do not give the second and final dose of TEMBEXA on Day 8 if ALT elevation is accompanied by clinical signs and symptoms of liver inflammation or increasing direct bilirubin, alkaline phosphatase, or International Normalized Ratio (INR) [see Adverse Reactions (6.1) and Drug Interactions (7.1)].

5.3 Diarrhea and Other Gastrointestinal Adverse Events

During the first 2 weeks of TEMBEXA therapy in 392 subjects, a composite term of diarrhea (all grade, all cause) occurred in 40% of TEMBEXA-treated subjects compared with 25% of subjects in the placebo control group. Treatment with TEMBEXA was discontinued in 5% of subjects for diarrhea (composite term) compared with 1% in the placebo control group. Additional gastrointestinal (GI) adverse events included nausea, vomiting, and abdominal pain; some of these adverse events required discontinuation of TEMBEXA [see Adverse Reactions (6.1) and Drug Interactions (7.1) and Nonclinical Toxicology (13.2)].

Monitor patients for GI adverse events including diarrhea and dehydration, provide supportive care, and if necessary, do not give the second and final dose of TEMBEXA.

5.4 Coadministration with Related Products

TEMBEXA should not be co-administered with intravenous cidofovir. Brincidofovir, a lipid-linked derivative of cidofovir, is intracellularly converted to cidofovir [see Clinical Pharmacology (12.3)].

5.5 Embryo-fetal Toxicity

Based on findings from animal reproduction studies, TEMBEXA may cause fetal harm when administered to pregnant individuals. TEMBEXA administration to pregnant rats and rabbits resulted in embryotoxicity, decreased embryo-fetal survival and/or structural malformations. These effects occurred in animals at systemic exposures less than the expected human exposure based on the recommended dose of TEMBEXA. Use an alternative therapy to treat smallpox during pregnancy, if feasible. Perform pregnancy testing in individuals of childbearing potential before initiation of TEMBEXA. Advise individuals of childbearing potential to avoid becoming pregnant and to use effective contraception during treatment with TEMBEXA and for at least 2 months after the last dose. Advise individuals of reproductive potential with partners of childbearing potential to use condoms during treatment with TEMBEXA and for at least 4 months after the last dose [see Use in Specific Populations (8.1, 8.3)].

5.6 Carcinogenicity

TEMBEXA is considered a potential human carcinogen. Mammary adenocarcinomas and squamous cell carcinomas occurred in rats at systemic exposures less than the expected human exposure based on the recommended dose of TEMBEXA [see Nonclinical Toxicology (13.1)]. Do not crush or divide TEMBEXA tablets. Avoid direct contact with broken or crushed tablets or oral suspension. If contact with skin or mucous membranes occurs, wash thoroughly with soap and water, and rinse eyes thoroughly with water [see How Supplied/Storage and Handling (16)].

5.7 Male Infertility

Based on testicular toxicity in animal studies, TEMBEXA may irreversibly impair fertility in individuals of reproductive potential [see Use in Specific Populations (8.3) and Nonclinical Toxicology (13.1)].

6 ADVERSE REACTIONS

The following clinically significant adverse reactions are described elsewhere in the labeling:

- Elevations in hepatic transaminases and bilirubin [see Warnings and Precautions (5.2)]
- Diarrhea and other GI adverse events [see Warnings and Precautions (5.3)]

6.1 Clinical Trials Experience

Because clinical trials are conducted under widely varying conditions, adverse reaction rates observed in the clinical trials of a drug cannot be directly compared to rates in the clinical trials of another drug and may not reflect the rates observed in practice.

The safety of TEMBEXA has not been studied in patients with smallpox disease.

The safety of TEMBEXA was evaluated in 392 adult subjects aged 18 to 77 years in Phase 2 and 3 randomized, placebo-controlled clinical trials. Of the subjects who received a 200 mg total weekly dose of TEMBEXA, 54% were male, 85% were White, 7% were Black/African American, 6% were Asian, and 10% were Hispanic or Latino. Twenty-one percent of subjects in the studies were age 65 or older. Of these 392 subjects, 85% received a 200 mg total weekly dose of TEMBEXA for at least 2 weeks.

Common Adverse Reactions

The most common adverse reactions (adverse events assessed as causally related by the investigator) experienced in the first 2 weeks of dosing with TEMBEXA were diarrhea and nausea. Adverse reactions that occurred in at least 2% of subjects in the TEMBEXA treatment group are shown in Table 2.

Table 2: Adverse Reactions (All Grades) Reported in ≥2% of Subjects
Adverse Reaction | TEMBEXA 200 mg; N=392; % | Placebo; N=208; %
Diarrheaa | 8 | 3
Nausea | 5 | 1
Vomitingb | 4 | 1
Abdominal painc | 3 | 2
Note: Only adverse reactions with onset in the first 2 weeks of treatment are presented.
a. Composite term includes: bowel movement irregularity, defecation urgency, diarrhea, fecal incontinence, and frequent bowel movements.
b. Composite term includes: vomiting and retching.
c. Composite term includes: abdominal discomfort, abdominal distention, abdominal pain, abdominal pain lower, abdominal pain upper, abdominal tenderness, and gastrointestinal pain.

Adverse Reactions Leading to Discontinuation of TEMBEXA

Fifteen subjects (4%) had their treatment with TEMBEXA discontinued due to adverse reactions. One subject had two adverse reactions; the other subjects had one reaction each. These adverse reactions were:

- Diarrhea (n=9)
- Nausea (n=3)
- Vomiting (n=1)
- Enteritis (n=1)
- ALT increased (n=1)
- Dyspepsia (n=1)

These adverse reactions were mild (Grade 1, n=1), moderate (Grade 2, n=7) or severe (Grade 3, n=8) in severity and resolved upon discontinuation of TEMBEXA.

Less Common Adverse Reactions

Clinically significant adverse reactions that were reported in <2% of subjects (and also occurred in 2 or more subjects) exposed to TEMBEXA and at rates higher than in subjects who received placebo are listed below:

- General and administration site: peripheral edema
- Metabolism and nutrition: decreased appetite
- Musculoskeletal and connective tissue: muscular weakness
- Nervous system: dysgeusia
- Skin and subcutaneous tissue: rash (includes rash, maculo-papular rash, pruritic rash)

Selected treatment-emergent laboratory values occurring during the first 2 weeks of treatment with TEMBEXA are presented in Table 3.

Table 3: Frequencies of Selected Laboratory Abnormalities
Laboratory Parameter Abnormalitya |  | TEMBEXA 200 mg; N=392 | Placebo; N=208
Alanine aminotransferase; (ALT)b | n | 382 | 203
Alanine aminotransferase; (ALT)b | Grade 2 (>3 to 5x ULN), (%) | 3 | 2
Alanine aminotransferase; (ALT)b | Grade 3 (>5 to 20x ULN), (%) | 2 | 1
Alanine aminotransferase; (ALT)b | Grade 4 (>20x ULN), (%) | 0 | 0
Aspartate aminotransferase; (AST)c | n | 380 | 201
Aspartate aminotransferase; (AST)c | Grade 2 (>3 to 5x ULN), (%) | 2 | 1
Aspartate aminotransferase; (AST)c | Grade 3 (>5 to 20x ULN), (%) | 1 | 0
Aspartate aminotransferase; (AST)c | Grade 4 (>20x ULN), (%) | 0 | 0
Total bilirubin | n | 382 | 203
Total bilirubin | Grade 2 (>1.5 to 3x ULN), (%) | 3 | 2
Total bilirubin | Grade 3 (>3 to 10x ULN), (%) | 1 | <1
Total bilirubin | Grade 4 (>10x ULN), (%) | 0 | 0
Serum creatinine | n | 383 | 205
Serum creatinine | Grade 2 (>1.5 to 3x ULN), (%) | 4 | 4
Serum creatinine | Grade 3 (>3 to 6x ULN), (%) | <1 | 0
Serum creatinine | Grade 4 (>6x ULN), (%) | 0 | 0
ULN = upper limit of normal
a. Frequencies are based on treatment-emergent laboratory abnormalities. Graded per Common Terminology Criteria for Adverse Events (CTCAE) version 4.03 toxicity grading criteria.
b. ALT >10x ULN occurred in one subject in the TEMBEXA group and no subjects in the placebo group.
c. No subjects reported AST >10x ULN.

Adverse Reactions in Pediatric Subjects

In 23 pediatric subjects aged 7 months to 17 years who received TEMBEXA in a randomized, placebo-controlled clinical trial, the adverse reactions and laboratory abnormalities observed with TEMBEXA were similar to adults [see Use in Specific Populations (8.4)].

7 DRUG INTERACTIONS

7.1 Effect of Other Drugs on TEMBEXA

Inhibitors for Organic Anion Transporting Polypeptide (OATP) 1B1 and 1B3

Concomitant use of TEMBEXA with OATP1B1 and 1B3 inhibitors (clarithromycin, cyclosporine, erythromycin, gemfibrozil, human immunodeficiency virus [HIV] and hepatitis C virus [HCV] protease inhibitors, rifampin [single dose]) increase brincidofovir AUC and Cmax which may increase TEMBEXA-associated adverse reactions [see Clinical Pharmacology (12.3)].

Where possible, consider alternative medications that are not OATP1B1 or 1B3 inhibitors. If concomitant use with TEMBEXA is necessary, increase monitoring for adverse reactions associated with TEMBEXA (elevations in transaminases and bilirubin, diarrhea, or other GI adverse events) [see Warnings and Precautions (5.2, 5.3)] and postpone the dosing of OATP1B1 or 1B3 inhibitors for at least 3 hours after TEMBEXA administration.

7.2 Vaccine Interactions

No vaccine-drug interaction studies have been performed in human subjects. Animal studies have indicated that coadministration of TEMBEXA at the same time as live smallpox vaccine (vaccinia virus) may reduce the immune response to the vaccine. It is also possible that TEMBEXA may reduce the immune response to replication-defective smallpox vaccine (modified vaccinia virus Ankara). The clinical impacts of these potential interactions on vaccine efficacy are unknown.

8 USE IN SPECIFIC POPULATIONS

8.1 Pregnancy

Risk Summary

Based on findings from animal reproduction studies, TEMBEXA may cause fetal harm when administered to pregnant individuals. Use an alternative therapy to treat smallpox during pregnancy, if feasible. There are no available data on the use of brincidofovir in pregnant individuals to evaluate for a drug-associated risk of major birth defects, miscarriage, and other adverse maternal and fetal outcomes. In animal reproduction studies, oral administration of brincidofovir to pregnant rats and rabbits during the period of organogenesis resulted in embryotoxicity and structural malformations. These effects occurred in animals at systemic exposures less than the expected human exposure based on the recommended dose of TEMBEXA (see Data).

The estimated background risk of major birth defects for the indicated population is unknown, and the estimated background risk of miscarriage for the indicated population is higher than the general population. All pregnancies have a background risk of birth defect, loss or other adverse outcomes. In the U.S. general population, the estimated background risk of major birth defects and miscarriage in clinically recognized pregnancies is 2% to 4% and 15% to 20%, respectively.

Data

Animal Data

In embryo-fetal development studies in rats and rabbits, pregnant animals were administered oral doses of brincidofovir up to 4.5 mg/kg/day from gestation days 7 to 20. Maternal toxicity in rats, characterized by decreases in food consumption and decreased body weight gain, was observed at doses of 1.5 and 4.5 mg/kg/day. These effects correlated with decreased fetal weights in rats given 4.5 mg/kg/day. Brincidofovir administration in rats was not associated with effects on intrauterine growth or survival at any dose, and there were no external malformations or developmental variations.

In rabbits, 4.5 mg/kg/day brincidofovir was associated with decreased maternal body weight and food consumption, decreased fetal body weight, increased late resorptions and morphological changes which included external, visceral and skeletal malformations and variations.

In the pre-/post-natal development study, administration of brincidofovir at doses of 0, 0.25, 1, and 4 mg/kg/day and 15 mg/kg twice weekly to pregnant rats from gestation day 7 to lactation day 20 resulted in pup toxicity at maternally toxic doses (4 mg/kg/day and 15 mg/kg twice weekly). Pup body weight and viability were decreased, and reproductive function of the pups was impaired as evidenced by a delay in sexual maturation, decreased testes and epididymal size, reduced mating and an increase in the number of days to mating as well as preimplantation loss.

All effects were observed at systemic exposures less than the expected human exposure based on the recommended dose of TEMBEXA.

8.2 Lactation

Risk Summary

Because of the potential for variola virus transmission through direct contact with the breastfed infant, breastfeeding is not recommended in patients with smallpox. There are no data on the presence of brincidofovir in human milk, the effects of the drug on the breastfed infant, or on milk production. Brincidofovir is present in animal milk (see Data).

Data

When brincidofovir was administered to lactating rats (4 mg/kg/day or 15 mg/kg twice weekly), brincidofovir was detected in milk but not in the plasma of nursing pups.

8.3 Females and Males of Reproductive Potential

Based on animal data, TEMBEXA may cause fetal harm [see Use in Specific Populations (8.1)].

Pregnancy Testing

Perform pregnancy testing in individuals of childbearing potential before initiation of TEMBEXA [see Dosage and Administration (2.1) and Warnings and Precautions (5.5)].

Contraception

Females

Advise individuals of childbearing potential to use effective contraception during treatment and for at least 2 months after the last dose of TEMBEXA [see Warnings and Precautions (5.5) and Use in Specific Populations (8.1)].

Males

Advise sexually active individuals with partners of childbearing potential to use condoms during treatment and for at least 4 months after last dose of TEMBEXA.

Infertility

Males

Based on testicular toxicity in animal studies, TEMBEXA may irreversibly impair fertility in individuals of reproductive potential [see Nonclinical Toxicology (13.1)].

8.4 Pediatric Use

As in adults, the effectiveness of TEMBEXA in smallpox infected pediatric patients, including neonates, is based solely on efficacy studies in animal models of orthopoxvirus disease. The recommended pediatric dosing regimen is expected to produce brincidofovir exposures that are comparable to those in adults based on a population pharmacokinetic modeling and simulation approach. The dosage for pediatric patients is based on weight [see Dosage and Administration (2.3) and Clinical Pharmacology (12.3)].

There have been 23 pediatric subjects aged 7 months to 17 years who received TEMBEXA in a randomized, placebo-controlled clinical trial. The safety in adult and pediatric subjects treated with TEMBEXA were similar [see Adverse Reactions (6.1)]. An additional 166 pediatric subjects aged 3 months to 18 years of age received TEMBEXA from uncontrolled studies and expanded access. The dosage of TEMBEXA in pediatric patients <3 months of age was based on modeling and simulations [see Clinical Pharmacology (12.3)].

8.5 Geriatric Use

Of the 392 subjects in the controlled clinical studies, 21% were ≥65 years of age and 1% were ≥75 years of age. The nature and severity of adverse events was comparable between subjects older and younger than 65 years. No alteration of dosing is recommended for patients ≥65 years of age [see Clinical Pharmacology (12.3)].

8.6 Renal Impairment

No dosage adjustment of TEMBEXA is required for patients with mild, moderate, or severe renal impairment or patients with end stage renal disease (ESRD) receiving dialysis [see Clinical Pharmacology (12.3)].

8.7 Hepatic Impairment

Perform hepatic laboratory testing in all patients before starting TEMBEXA and while receiving TEMBEXA, as clinically appropriate. No dosage adjustment is required for patients with mild, moderate, or severe hepatic impairment (Child-Pugh Class A, B, or C) [see Warnings and Precautions (5.2), Adverse Reactions (6.1), and Clinical Pharmacology (12.3)].

10 OVERDOSAGE

There is no clinical experience with overdosage of TEMBEXA. In the event of an overdose, monitor patients for adverse effects and provide appropriate supportive care.

11 DESCRIPTION

TEMBEXA (brincidofovir) tablets, 100 mg, for oral use are immediate release film-coated tablets containing the following inactive ingredients: Colloidal Silicon Dioxide, Crospovidone, FD&C Blue #1/Brilliant Blue FCF Aluminum Lake, FD&C Blue #2/Indigo Carmine Aluminum Lake, Magnesium Stearate, Mannitol, Microcrystalline Cellulose, Polyethylene Glycol, Polyvinyl Alcohol, Purified Water, Silicified Microcrystalline Cellulose, Talc and Titanium Dioxide.

TEMBEXA (brincidofovir) oral suspension, 10 mg/mL, is an aqueous based, preserved, orally dosed suspension. The inactive ingredients are: Citric Acid Anhydrous, Lemon Lime Flavor, Microcrystalline Cellulose and Carboxymethyl Cellulose Sodium, Purified Water, Simethicone 30% Emulsion, Sodium Benzoate, Sucralose, Trisodium Citrate Anhydrous, and Xanthan Gum.

Brincidofovir is an orthopoxvirus nucleotide analog DNA polymerase inhibitor and a lipid conjugate of the nucleotide analog cidofovir and is indicated for the treatment of human smallpox disease.

The full chemical name is: Phosphonic acid, P-[[(1S)-2-(4-amino-2-oxo-1(2H)-pyrimidinyl)-1-(hydroxymethyl)ethoxy]methyl]-, mono[3-(hexadecyloxy)propyl] ester.

The molecular formula of brincidofovir is C27H52N3O7P and the relative molecular mass is 561.70.

The structure is shown below.

Brincidofovir is a white to off-white crystalline powder as a free acid and practically insoluble in water.

12 CLINICAL PHARMACOLOGY

12.1 Mechanism of Action

Brincidofovir is an antiviral drug against variola (smallpox) virus [see Microbiology (12.4)].

12.2 Pharmacodynamics

Brincidofovir and its active metabolite cidofovir diphosphate exposure-response relationships and time course of pharmacodynamic responses are unknown.

Cardiac Electrophysiology

TEMBEXA does not prolong the QT interval at the anticipated therapeutic exposure.

12.3 Pharmacokinetics

Brincidofovir is a prodrug that is converted intracellularly to cidofovir, which is subsequently phosphorylated to cidofovir diphosphate, the active antiviral moiety, following oral administration. Brincidofovir plasma exposures do not accumulate after repeat doses. The metabolite cidofovir diphosphate reaches maximum concentration at 47 hours (23 to 311 hours) following administration of the recommended dose, with a mean (CV%) half-life of 113 hours (34.2%). The pharmacokinetic properties of brincidofovir following administration of TEMBEXA are provided in Table 4. The pharmacokinetic parameters of brincidofovir and cidofovir diphosphate following administration of TEMBEXA at the recommended dose are provided in Table 5.

Table 4: Pharmacokinetic Properties of Brincidofovira
Absorption
Bioavailability | Oral suspension | 16.8%
Bioavailability | Tablet | 13.4%
Tmaxb |  | 3 hours (2 to 8 hours)
Effect of food on TEMBEXA Tablet (relative to fasting)c |  | - AUCinf decreased by 31% - Cmax decreased by 49%
Distribution
% Bound to human plasma proteins |  | >99.9%
Blood-to-plasma ratio (drug or drug-related materials)d |  | 0.48 to 0.61
Apparent Volume of distribution, L |  | 1230
Elimination
Apparent Clearance, L/hr |  | 44.1
Mean terminal half-life (t1/2), hr |  | 19.3
Metabolism
Metabolic pathways |  | hydrolysis, CYP4F2
Metabolites |  | cidofovir and cidofovir diphosphate (active)
Excretion
% of dose excreted in urined |  | 51%, as metabolites
% of dose excreted in fecesd |  | 40%, as metabolites
a. Healthy adults.
b. Administered under fasted conditions.
c. Low-fat meal: ~400 calories, with ~25% calories from fat. No clinically meaningful change in intracellular concentrations of cidofovir diphosphate were seen when TEMBEXA Tablet was administered with a low-fat meal. The effect of food on TEMBEXA oral suspension has not been studied.
d. Following administration of radiolabeled brincidofovir.

Table 5: Single-Dose Pharmacokinetic Parameters of Brincidofovir and Cidofovir Diphosphatea
PK Parameter | Geometric Mean (%CV)
PK Parameter | Brincidofovir | Cidofovir diphosphate
Cmax | 480 ng/mL (70%) | 9.7 pg/10^6 cells (75%)
AUCtau | 3400 ng‧hr/mL (58%) | 1200 pg‧hr/10^6 cells (75%)
AUC = area under the time concentration curve; Cmax = maximum concentration; CV = coefficient of variation.
a. Healthy adults

Metabolism

Brincidofovir is metabolized by hydrolysis of the phosphoester bond to form cidofovir. Cidofovir is subsequently phosphorylated to form cidofovir diphosphate. Brincidofovir is also carboxylated at the terminal carbon by Cytochrome P450 (CYP) 4F2, followed by subsequent CYP-mediated oxidations and multiple cycles of fatty acid beta-oxidation. The major inactive metabolites formed via these pathways are CMX103 (3-hydroxypropyl ester of cidofovir) and CMX064 (4-(3-propoxy)butanoic acid ester of cidofovir).

Genetic and chemical inhibition of acid sphingomyelinase enzyme activity in multiple human cell lines resulted in substantially lower concentrations of cidofovir and cidofovir diphosphate (the active drug), compared to controls with functional acid sphingomyelinase enzyme activity. Findings show acid sphingomyelinase plays a major role in the hydrolysis of brincidofovir to cidofovir in these cell lines. Based on in vitro data, acid sphingomyelinase deficiency may reduce the ability to convert brincidofovir to cidofovir and cidofovir diphosphate; however, the clinical relevance of this finding is unknown.

Comparison of Animal and Human Pharmacokinetic Data to Support Effective Human Dose Selection

Because the effectiveness of TEMBEXA cannot be tested in humans, a comparison of brincidofovir and cidofovir diphosphate exposures achieved in human subjects to those observed in animal models of orthopoxvirus infection (rabbits infected with rabbitpox virus, and mice infected with ectromelia virus) in efficacy studies was necessary to support the dose and regimen of 200 mg once a week for 2 doses for treatment of smallpox disease in humans. Humans achieve greater systemic exposures (AUC and Cmax) of brincidofovir and greater than or equal to intracellular concentrations of cidofovir diphosphate following a 200 mg once a week dose when compared with therapeutic exposure in the animal models [see Clinical Studies (14)].

Specific Populations

No clinically meaningful differences in the pharmacokinetics of brincidofovir were observed based on age, sex, race, reduced activity in the CYP4F2 enzyme, renal impairment including ESRD with or without dialysis (based on estimated glomerular filtration rate [GFR]), or hepatic impairment (Child-Pugh Class B, C).

Patients Requiring Hemodialysis

The AUC and Cmax of brincidofovir and its metabolite cidofovir were comparable between subjects requiring hemodialysis whether on- or off-dialysis.

Pediatric Patients

The pharmacokinetics of TEMBEXA suspension has been evaluated in pediatric individuals. Pharmacokinetic simulation was used to derive dosing regimens that are predicted to provide pediatric patients, including neonates, with exposures comparable to the observed exposure in adults receiving TEMBEXA tablets.

Drug Interaction Studies

Clinical Studies

OATP1B1 and 1B3 Inhibitors: A single 600 mg oral cyclosporine (OATP1B1 and 1B3 inhibitor) dose increased the mean brincidofovir AUC0-inf and Cmax by 374% and 269%, respectively, when administered concomitantly with TEMBEXA.

CYP Substrates: No clinically significant differences in the pharmacokinetics of midazolam (sensitive CYP3A substrate) were observed when administered concomitantly with TEMBEXA.

P-gp Substrates: No clinically significant differences in the pharmacokinetics of dabigatran etexilate (P-gp substrate) were observed when administered concomitantly with TEMBEXA.

In vitro Studies Where Drug Interaction Potential Was Not Further Evaluated Clinically

CYP Enzymes: Brincidofovir is a direct and reversible inhibitor of CYP1A2, CYP2B6, CYP2C8, CYP2C9, CYP2C19, CYP2D6, CYP4F2. Brincidofovir is not an inducer of CYP1A2, CYP2B6 or CYP3A.

Transporter Systems: Brincidofovir is an inhibitor of Breast Cancer Resistance Protein (BCRP), multidrug resistance-associated protein 2 (MRP2), bile salt export pump (BSEP), OATP1B1, Organic Anion Transporter 1 (OAT1), and OAT3. Brincidofovir is not an inhibitor of OATP1B3, Organic Cation Transporter 2 (OCT2), multidrug and toxin extrusion protein 1 (MATE1), or MATE2-K in vitro.

12.4 Microbiology

Mechanism of Action

Brincidofovir is a lipid conjugate of cidofovir, an acyclic nucleotide analog of deoxycytidine monophosphate. The lipid conjugate is designed to mimic a natural lipid, lysophosphatidylcholine, and thereby use endogenous lipid uptake pathways. Once inside cells, the lipid ester linkage of brincidofovir is cleaved to liberate cidofovir, which is then phosphorylated to produce the active antiviral, cidofovir diphosphate. Based on biochemical and mechanistic studies using recombinant vaccinia virus E9L DNA polymerase, cidofovir diphosphate selectively inhibits orthopoxvirus DNA polymerase-mediated viral DNA synthesis. Incorporation of cidofovir into the growing viral DNA chain results in reductions in the rate of viral DNA synthesis.

Activity in Cell Culture

The median 50% effective concentration (EC50) of brincidofovir against variola virus was 0.11 μM (range 0.05 to 0.21 μM) across 5 variola virus strains chosen to represent 5 distinct variola virus DNA polymerase genotypes. The median EC50 values of brincidofovir against rabbitpox, ectromelia, vaccinia, and monkeypox viruses were 1.10 μM (n=4, 0.5-1.89 μM), 0.33 μM (n=5, 0.12-0.51 μM), 0.17 μM (n=22, 0.004-1.2 μM), and 0.074 μM (n=2, 0.023-0.12 μM), respectively.

Non-antagonistic antiviral activity of brincidofovir and tecovirimat has been demonstrated in cell culture and animal models.

Resistance

There are no known instances of naturally occurring brincidofovir resistant orthopoxviruses, although brincidofovir resistance may develop under drug selection. Cell culture studies have shown that certain amino acid substitutions in the target viral DNA polymerase protein can confer reductions in brincidofovir antiviral activity. The possibility of resistance to brincidofovir should be considered in patients who either fail to respond to therapy or who develop recrudescence of disease after an initial period of responsiveness.

Cross-resistance

Cross-resistance between brincidofovir and tecovirimat is not expected based on their distinct mechanisms of action. Where tested, orthopoxvirus isolates resistant to tecovirimat have not been resistant to brincidofovir and/or cidofovir and vice versa.

13 NONCLINICAL TOXICOLOGY

13.1 Carcinogenesis, Mutagenesis, Impairment of Fertility

Carcinogenesis and Mutagenesis

Palpable masses occurred in rats with high frequency after as few as 26 oral doses of brincidofovir at systemic exposures less than the expected human exposure based on the recommended dose of TEMBEXA. The masses diagnosed as mammary adenocarcinomas, carcinoma in squamous cell, Zymbal’s gland, uterus and small intestine and hemangiosarcomas in mesenteric and mediastinal lymph node, liver and abdominal cavity were observed in rats following long term (13-weeks and 26-weeks) dosing studies. No tumors occurred in rats after 9 twice-weekly intravenous doses, although rats were only followed for 14 days after the last administration. Based on these data and the unknown translation of nonclinical findings to clinical risk, TEMBEXA is considered a potential human carcinogen.

Brincidofovir was negative in a bacterial mutagenicity (Ames) assay and an in vivo micronucleus assay in mice. Brincidofovir was positive for increased structural chromosomal aberrations in the absence of metabolic activation in an in vitro assay.

Impairment of Fertility

In chronic dosing studies with orally administered brincidofovir, testicular effects were seen in both rats and monkeys. Monkeys administered twice weekly doses of brincidofovir via oral gavage for 9 months exhibited atrophy of the seminiferous tubules and hypospermia in the epididymides. Based on sperm analysis and histopathology, these findings demonstrated a trend towards recovery after a 6 month, post-dosing period. Rats administered brincidofovir via oral gavage twice weekly for 13 weeks exhibited decreased testes weights, depletion of spermatogenesis and hypospermia. Unlike in the monkey, recovery was not demonstrated in the rats following a 12-week post-dosing period.

In a rat fertility and early embryonic development study, administration of brincidofovir once daily beginning 15 days before cohabitation, during cohabitation and continuing through gestation day 7 resulted in decreased embryonal viability at 0.25 mg/kg/day, a dose that did not cause maternal toxicity. Male rats dosed twice weekly by oral gavage for 10 to 19 weeks had reduced sperm motility and a decrease in total sperm count. These effects resulted in reduced fertility during the first cohabitation period, and infertility during the second cohabitation period.

Brincidofovir exposures in both monkeys and rats were less than exposures seen in humans administered 200 mg brincidofovir. Studies conducted using intravenous brincidofovir to achieve clinically relevant exposures demonstrated diminished but ongoing spermatogenesis in the tubules of rats 15 weeks after administration of 3 doses of brincidofovir administered once weekly. The testicular pathology appears to be an effect on the mitotic spermatogonia.

13.2 Animal Toxicology and/or Pharmacology

Gastrointestinal Toxicity: GI toxicity is the dose-limiting toxicity of orally-administered brincidofovir. Signs of GI toxicity include decreased body weight and food consumption, fecal changes (absent, nonformed, or liquid feces), and dehydration. Dose-limiting GI events, diagnosed as gastropathy and enteropathy or enteritis, were observed following daily oral administration of brincidofovir in mice and monkeys. A single dose study to characterize the pathological dynamics of GI toxicity and potential reversibility revealed a dose responsive enteritis in rats, which reversed in surviving animals by 14 days post-dose. Subsequent animal studies used twice weekly oral administration to reflect anticipated clinical use and no dose-limiting GI toxicity was observed.

Aminotransferase Elevations: Increases in ALT (2- to 5-fold) were observed in both rodent and nonrodent species in nonclinical toxicology studies of orally administered brincidofovir. The changes seen with oral dosing appeared with highest frequency in monkeys, followed by mice and then rats. ALT elevations did not correlate with dose concentration and reversed after cessation of dosing. There were no gross or microscopic hepatic changes that correlated with the ALT increases.

14 CLINICAL STUDIES

Overview

The effectiveness of TEMBEXA for treatment of smallpox disease has not been determined in humans because adequate and well-controlled field trials have not been feasible and inducing smallpox disease in humans to study the efficacy of the drug is not ethical. Therefore, the effectiveness of TEMBEXA for treatment of smallpox disease was established based on results of adequate and well-controlled animal efficacy studies of rabbits and mice infected with species specific non-variola orthopoxviruses. Survival rates observed in the animal studies may not be predictive of survival rates in clinical practice.

Study Design

Efficacy studies were conducted in the rabbitpox model (New Zealand White rabbits infected with rabbitpox virus) and the mousepox model (BALB/c mice infected with ectromelia virus).

The primary efficacy endpoint for these studies was survival. Survival was monitored for 4 to 5 times the mean time to death for untreated animals in each model.

In the rabbitpox study, rabbits were lethally challenged intradermally with 600 plaque-forming units of rabbitpox virus; brincidofovir was administered orally with a regimen of 20/5/5 mg/kg (administered every 48 hours for 3 doses) with brincidofovir treatment initiated on 3, 4, 5, or 6 days post-challenge. The timing of brincidofovir dosing was intended to assess efficacy when treatment is initiated after animals have developed clinical signs of disease, specifically fever in rabbits. Clinical signs of disease were evident in some animals at Day 3 post-challenge but were evident in all animals by Day 4 post-challenge.

In the mousepox study, mice were lethally challenged intranasally with 200 plaque-forming units of ectromelia virus; brincidofovir was administered orally with a regimen of 20/5/5 mg/kg or 10/5/5 mg/kg (administered every 48 hours for 3 doses) with brincidofovir treatment initiated on 4, 5, 6, or 7 days post-challenge. All animals had detectable viremia by 4 days post-challenge. In the mousepox model, a clinically evident sign of disease could not be identified to use as a trigger to initiate treatment.

Study Results

Treatment with brincidofovir resulted in statistically significant improvement in survival relative to placebo, except when the 10/5/5 mg/kg regimen was initiated at Day 6 post-challenge in the mousepox study (Table 6).

Table 6: Survival Rates in Brincidofovir Treatment Studies in the Rabbitpox and Mousepox Models
Dose Regimen (mg/kg) | Treatment Initiation Day | Survival % (# survived/n) |  | Survival Rate Difference; (95% CI)a | p-valueb
Dose Regimen (mg/kg) | Treatment Initiation Day | Placebo | Brincidofovir | Survival Rate Difference; (95% CI)a | p-valueb
Rabbitpoxc
Study 1 | Day 4 | 29%; (8/28) | 90% (26/29) | 61% (36%, 79%) | <0.0001
Study 1 | Day 5 | 29%; (8/28) | 69% (20/29) | 40% (12%, 63%) | 0.0014
Study 1 | Day 6 | 29%; (8/28) | 69% (20/29) | 40% (12%, 63%) | 0.0014
Mousepoxd
Study 2 | Day 4 | 13%; (4/32) | 78% (25/32) | 66% (44%, 82%) | <0.0001
Study 2 | Day 5 | 13%; (4/32) | 66% (21/32) | 53% (29%, 72%) | <0.0001
Study 2 | Day 6 | 13%; (4/32) | 34% (11/32) | 22% (1%, 43%) | 0.0233e
a. Survival percentage with brincidofovir-treated animals minus survival percentage in placebo-treated animals. Exact confidence intervals are presented.
b. P-value is from 1-sided Boschloo test compared with placebo.
c. 20/5/5 mg/kg (fully effective dose in the rabbitpox model)
d. 10/5/5 mg/kg (fully effective dose in the mousepox model)
e. P-value is not significant at the one-sided alpha of 0.0125.

16 HOW SUPPLIED/STORAGE AND HANDLING

TEMBEXA Tablets:

Tablets are blue, modified-oval shape, film-coated tablets debossed with BCV on one side and 100 on the other side and packaged into blister cards. Each blister cavity contains one film-coated tablet containing 100 mg of brincidofovir. The blister card is placed in a child-resistant wallet. Each wallet (NDC 64678-010-01) contains one (1) blister card with a total of 4 film-coated tablets.

Store at 20°C to 25°C (68°F to 77°F); excursions permitted from 15°C to 30°C (59°F to 86°F) [see USP Controlled Room Temperature].

Do not divide, break, or crush the tablets. Avoid direct contact with broken or crushed tablets. If contact with skin or mucous membranes occurs, wash thoroughly with soap and water, and rinse eyes thoroughly with water [see Warnings and Precautions (5.6)].

TEMBEXA Oral Suspension:

Aqueous based, preserved white to off-white opaque, lemon lime flavored suspension containing 10 mg/mL of brincidofovir packaged into a high density polyethylene bottle with a low density polyethylene press-in bottle adaptor (PIBA) inserted into the bottle. The bottle is capped by a child-resistant closure. Each bottle is filled to deliver 65 mL (NDC 64678-012-01) and 45 mL (NDC 64678-012-03) of brincidofovir.

Store at 20°C to 25°C (68°F to 77°F); excursions permitted from 15°C to 30°C (59°F to 86°F) [see USP Controlled Room Temperature]. Do not freeze.

Avoid direct contact with oral suspension. If contact with skin or mucous membranes occurs, wash thoroughly with soap and water, and rinse eyes thoroughly with water [see Warnings and Precautions (5.6)].

17 PATIENT COUNSELING INFORMATION

Advise the patient to read the FDA-approved patient labeling (Patient Information).

Efficacy Based on Animal Models Alone

Inform patients that the efficacy of TEMBEXA is based solely on efficacy studies demonstrating a survival benefit in animals and that the effectiveness of TEMBEXA has not been tested in humans with smallpox disease [see Clinical Studies (14)].

Elevations of Hepatic Transaminases and Bilirubin

Inform patients of the need for liver monitoring before treatment with TEMBEXA and during treatment if signs or symptoms of liver injury occur. Advise patients to report symptoms that may indicate liver injury, including right upper abdominal discomfort, dark urine, or jaundice [see Warnings and Precautions (5.2)].

Diarrhea and Other Gastrointestinal Adverse Events

Inform patients of the risk of diarrhea and other GI adverse events (nausea, vomiting, and abdominal pain) while taking TEMBEXA. Advise patients to inform their healthcare provider if they develop severe diarrhea or other severe GI symptoms [see Warnings and Precautions (5.3) and Adverse Reactions (6.1)].

Important Drug Interactions

Inform patients that TEMBEXA may interact with some drugs. If concomitant use of OATP1B1 and 1B3 inhibitors with TEMBEXA is necessary, advise patients to postpone the dosing of these medicines for at least 3 hours after TEMBEXA administration [see Drug Interactions (7.1) and Clinical Pharmacology (12.3)].

Embryo-fetal Toxicity

Advise pregnant individuals and individuals of childbearing potential of the risk to a fetus and to inform their healthcare provider of a known or suspected pregnancy. Advise individuals of childbearing potential to use effective contraception during treatment with TEMBEXA and for at least 2 months after the last dose. Due to animal findings of testicular toxicity, advise individuals of reproductive potential with partners of childbearing potential to use condoms during treatment with TEMBEXA and for at least 4 months after the last dose [see Warnings and Precautions (5.5, 5.7) and Use in Specific Populations (8.3)].

Infertility

Advise individuals of reproductive potential that treatment with TEMBEXA may deplete sperm, resulting in infertility [see Use in Specific Populations (8.3) and Nonclinical Toxicology (13.1)].

Lactation

Instruct individuals with smallpox not to breastfeed their infant because of the risk of passing variola virus to the breastfed infant [see Use in Specific Populations (8.2)].

Important Administration Instructions for Oral Suspension

Instruct patients or caregivers to use an oral dosing syringe to correctly measure the prescribed amount of medication. Oral dosing syringes may be obtained from the pharmacy. Refer to instructions above for administration of TEMBEXA oral suspension through enteral tubes [see Dosage and Administration (2.2)].

Advise patients taking the oral suspension to discard unused portion after completion of the 2 prescribed doses.

Handling

Advise patients not to divide, break, or crush tablets. Advise patients to avoid direct contact with broken or crushed tablets and oral suspension. If contact with skin or mucous membranes occurs, inform patients to wash thoroughly with soap and water, and rinse eyes thoroughly with water [see Dosage and Administration (2.2) and How Supplied/Storage and Handling (16)].

Manufactured for Emergent BioDefense
Operations Lansing LLC

3500 North Martin Luther King Jr Blvd
Lansing, MI 48906

Patient Package Insert

PATIENT INFORMATION

TEMBEXA (tem-BEKS-uh)
(brincidofovir)
tablets

TEMBEXA (tem-BEKS-uh)
(brincidofovir)
oral suspension

What is TEMBEXA?

TEMBEXA is a prescription medicine used to treat smallpox disease caused by a type of virus called variola virus in adults, children, and infants.

- The effectiveness of TEMBEXA has been studied only in animals with orthopoxvirus diseases. There have been no human studies in people who have smallpox disease.
- The safety of TEMBEXA has been studied in adults and children older than 3 months.
- TEMBEXA may not work in people who have a weakened immune system.
- The safety and effectiveness of TEMBEXA is not known for diseases other than human smallpox disease.

Before taking TEMBEXA, tell your healthcare provider about all your medical conditions, including if you:

- are pregnant or plan to become pregnant. TEMBEXA can harm your unborn baby. Tell your healthcare provider if you become pregnant or think that you may be pregnant during treatment with TEMBEXA.
  - Your healthcare provider should check to see if you are pregnant before you begin treatment with TEMBEXA.
  - Your healthcare provider may use another medicine to treat your smallpox if you are pregnant.
  - Individuals who can get pregnant should use effective birth control during treatment with TEMBEXA and for at least 2 months after the last dose.
  - TEMBEXA may harm your sperm. If you are sexually active with an individual who can become pregnant, you should use condoms during treatment with TEMBEXA and for at least 4 months after the last dose.
- are breastfeeding or plan to breastfeed. Breastfeeding is not recommended for individuals with smallpox because of the risk of passing variola virus to the breastfed infant.

Tell your healthcare provider about all the medicines you take, including prescription and over-the-counter medicines, vitamins, and herbal supplements. Some medicines interact with TEMBEXA causing side effects. Keep a list of your medicines to show your healthcare provider and pharmacist.

- You can ask your healthcare provider or pharmacist for a list of medicines that interact with TEMBEXA.
- Do not start taking a new medicine without telling your healthcare provider. Your healthcare provider can tell you if it is safe to take TEMBEXA with other medicines.

How should I take TEMBEXA?

- Take TEMBEXA exactly as your healthcare provider tells you.
- It is important to take TEMBEXA one time a week for 2 doses (on Day 1 and Day 8), as instructed. Do not miss or skip a dose of TEMBEXA.
- TEMBEXA tablets can be taken on an empty stomach or with a low-fat meal (around 400 calories, with about 25% of calories from fat). Talk to your healthcare provider about examples of foods that you can eat for a low-fat meal.
- TEMBEXA oral suspension can be taken on an empty stomach.
- For adults and children taking the TEMBEXA oral suspension, shake the suspension bottle well before each use. Use an oral dosing syringe to correctly measure your dose. Ask your pharmacist for an oral dosing syringe if you do not have one. Only take the amount prescribed to you. Throw away (discard) any unused portion.
- For people who are not able to swallow: You may give TEMBEXA oral suspension through a naso-gastric (NG) or gastrostomy (“g”) tube to someone who is not able to swallow, using the following instructions:
  - Draw up the prescribed amount (dose) of TEMBEXA oral suspension using a catheter-tip syringe with mL markings on it.
  - Give the dose through the naso-gastric tube or gastrostomy tube.
  - Refill the catheter-tip syringe with 3 mL of water and shake the syringe. Give the contents of the syringe through the naso-gastric tube or gastrostomy tube.
  - Flush with water before and after administration.
- Stay under the care of your healthcare provider during treatment with TEMBEXA.
- Do not change your dose or stop taking TEMBEXA without talking to your healthcare provider.
- Swallow TEMBEXA tablets whole. Do not divide, break, or crush TEMBEXA tablets. Do not touch broken or crushed tablets or oral suspension. If you touch TEMBEXA, wash your hands very well with soap and water. If you get TEMBEXA in your eyes, rinse your eyes well with water.
- If you take too much TEMBEXA, call your healthcare provider or go to the nearest hospital emergency room right away.

What are the possible side effects of TEMBEXA?

TEMBEXA may cause serious side effects, including:

- Liver problems. Your healthcare provider should perform blood tests to check your liver before you start taking TEMBEXA and during treatment with TEMBEXA for any signs or symptoms of liver problems. Call your healthcare provider right away if you have the following symptoms:
  - Stomach discomfort in the upper right side
  - Dark urine
  - Yellowing of your skin or the whites of your eyes (jaundice)
- Diarrhea. Diarrhea is common in people who take TEMBEXA but can also be serious. Call your healthcare provider right away if you develop diarrhea with 4 or more stools per day over your usual daily number of stools.

The most common side effects of TEMBEXA include:

- Diarrhea
- Nausea
- Stomach pain
- Vomiting

TEMBEXA may cause low sperm counts and affect the ability to conceive children. Talk to your healthcare provider if you have concerns about fertility.

These are not all the possible side effects of TEMBEXA. Call your doctor for medical advice about side effects. You may report side effects to FDA at 1-800-FDA-1088.

How should I store TEMBEXA?

- Store TEMBEXA tablets and oral suspension at room temperature between 68°F to 77°F (20°C to 25°C).
- Do not freeze TEMBEXA oral suspension.
- Keep TEMBEXA in its original container.

Keep TEMBEXA and all other medicines out of the reach of children.

General information about the safe and effective use of TEMBEXA.

Medicines are sometimes prescribed for purposes other than those listed in a Patient Information leaflet. Do not use TEMBEXA for a condition for which it was not prescribed. Do not give TEMBEXA to other people, even if they have the same symptoms that you have. It may harm them. You can ask your pharmacist or healthcare provider for information about TEMBEXA that is written for health professionals.

What are the ingredients in TEMBEXA?

Active ingredient: brincidofovir

Inactive ingredients:

- Tablets: Colloidal Silicon Dioxide, Crospovidone, FD&C Blue #1/Brilliant Blue FCF Aluminum Lake, FD&C Blue #2/Indigo Carmine Aluminum Lake, Magnesium Stearate, Mannitol, Microcrystalline Cellulose, Polyethylene Glycol, Polyvinyl Alcohol, Purified Water, Silicified Microcrystalline Cellulose, Talc, Titanium Dioxide.
- Oral Suspension: Citric Acid Anhydrous, Lemon Lime Flavor, Microcrystalline Cellulose and Carboxymethyl Cellulose Sodium, Purified Water, Simethicone 30% Emulsion, Sodium Benzoate, Sucralose, Trisodium Citrate Anhydrous, Xanthan Gum.

Manufactured for Emergent BioDefense Operations Lansing LLC

3500 North Martin Luther King Jr Blvd
Lansing, MI 48906

For more information, call 1-877-246-8472.

This Patient Information has been approved by the U.S. Food and Drug Administration. Issued: 10/2022

PACKAGE/LABEL PRINCIPAL DISPLAY PANEL

For oral use

Rx Only

TEMBEXA®

brincidofovir

Oral Suspension, 10 mg/mL

Contents: 65 mL

NDC 64678-012-01

For oral use

Rx Only

TEMBEXA®

brincidofovir

Oral Suspension, 10 mg/mL

Contents: 65 mL

PACKAGE/LABEL PRINCIPAL DISPLAY PANEL

For oral use

Rx Only

TEMBEXA®

brincidofovir

Oral Suspension, 10 mg/mL

Contents: 45 mL

See Full
Prescribing Information
For TEMBEXA Inside.

NDC 64678-012-03

For oral use

Rx Only

TEMBEXA®

brincidofovir

Oral Suspension, 10 mg/mL

Contents: 45 ml

PACKAGE/LABEL PRINCIPAL DISPLAY PANEL

For oral use

Rx Only

TEMBEXA®

brincidofovir

Oral Suspension, 10 mg/mL

Contents: 45 mL

See Full
Prescribing Information
For TEMBEXA Inside.

For Strategic National
Stockpile Use Only

NDC 64678-012-04

For oral use

Rx Only

TEMBEXA®

brincidofovir

Oral Suspension, 10 mg/mL

Contents: 45 mL